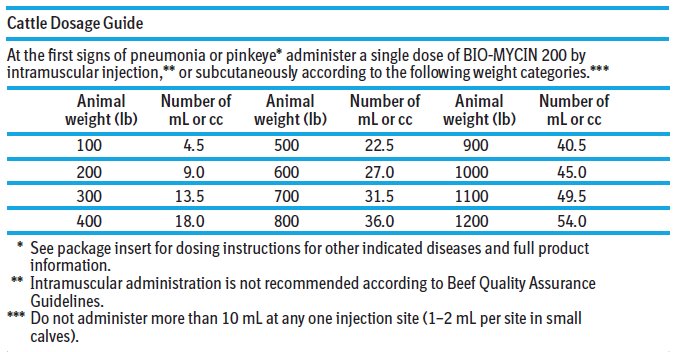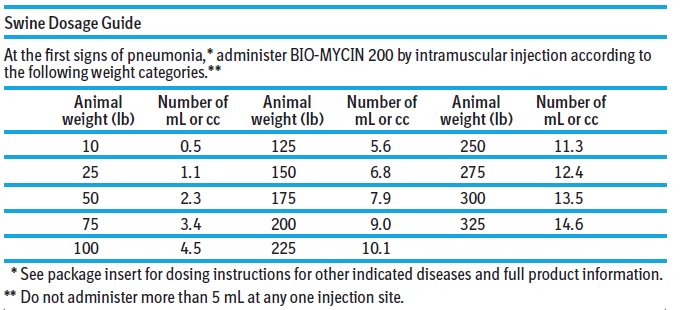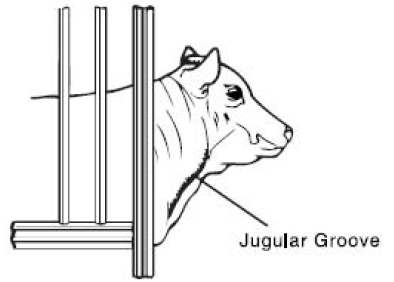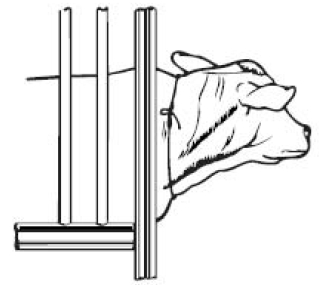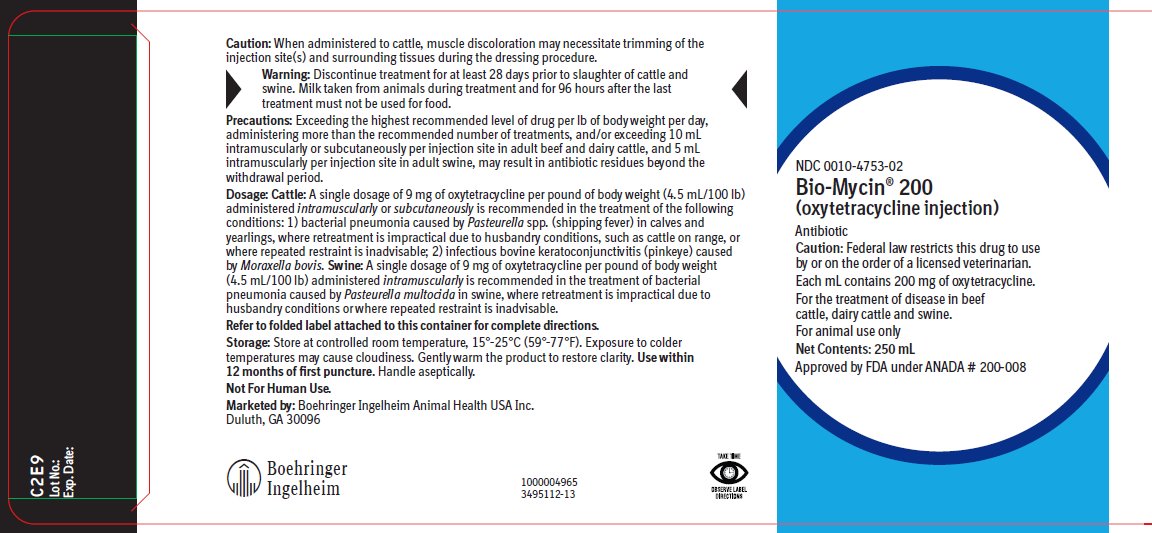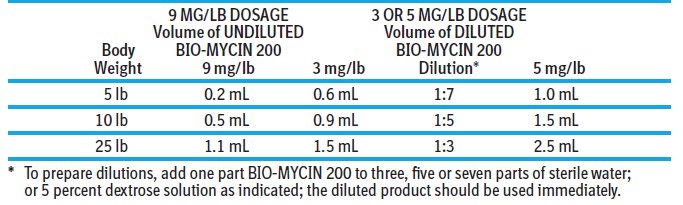 DRUG LABEL: Bio-Mycin 200
NDC: 0010-4753 | Form: INJECTION
Manufacturer: Boehringer Ingelheim Animal Health USA Inc.
Category: animal | Type: PRESCRIPTION ANIMAL DRUG LABEL
Date: 20250327

ACTIVE INGREDIENTS: OXYTETRACYCLINE 200 mg/1 mL
INACTIVE INGREDIENTS: POLYETHYLENE GLYCOL 400 300 mg/1 mL; SODIUM FORMALDEHYDE SULFOXYLATE 5.0 mg/1 mL; MAGNESIUM OXIDE 17.0 mg/1 mL; 2-AMINOETHANOL; WATER

Bio-Mycin® 200
(oxytetracycline injection)

Approved by FDA under ANADA # 200-008

Antibiotic

Caution: Federal law restricts this drug to use by or on the order of a licensed veterinarian.

DESCRIPTION

Each mL contains 200 mg oxytetracycline.

For the treatment of disease in beef cattle, dairy cattle and swine.

For animal use only

Read entire insert carefully before using this product.

BIO-MYCIN 200 is a sterile, ready-to-use solution of the broad spectrum antibiotic oxytetracycline by injection. Oxytetracycline injection administered to cattle or swine for the treatment of bacterial pneumonia at a dosage of 9 mg of oxytetracycline per lb of body weight has been demonstrated in clinical trials to be as effective as 2 or 3 repeated, daily treatments at 3-5 mg/lb of body weight. Each mL contains 200 mg of oxytetracycline; magnesium oxide 1.7% w/v; sodium formaldehyde sulfoxylate 0.5% w/v; polyethylene glycol 400 30% w/v; monoethanolamine to adjust pH; water for injection USP qs. The antibiotic activity of oxytetracycline is not appreciably diminished in the presence of body fluids, serum or exudates.

Caution:

When administered to cattle, muscle discoloration may necessitate trimming of the injection site(s) and surrounding tissues during the dressing procedure.

Warning:

Discontinue treatment at least 28 days prior to slaughter of cattle and swine. Milk taken from animals during treatment and for 96 hours after the last treatment must not be used for food.

Rapid intravenous administration may result in animal collapse. Oxytetracycline should be administered intravenously slowly over a period of at least 5 minutes.

Precautions:

Exceeding the highest recommended dosage level of drug per pound of body weight per day, administering more than the recommended number of treatments and/or exceeding 10 mL intramuscularly or subcutaneously per injection site in adult beef cattle and dairy cattle, and 5 mL intramuscularly per injection site in adult swine, may result in antibiotic residues beyond the withdrawal period.

At the first sign of any adverse reaction, discontinue use of product and seek the advice of your veterinarian. Some of the reactions may be attributed either to anaphylaxis (an allergic reaction) or to cardiovascular collapse of unknown cause. Shortly after injection treated animals may have transient hemoglobinuria resulting in darkened urine.

As with all antibiotic preparations, use of this drug may result in overgrowth of nonsusceptible organisms, including fungi. A lack of response by the treated animal, or the development of new signs, may suggest that an overgrowth of nonsusceptible organisms has occurred. If any of these conditions occur, consult your veterinarian.

Since bacteriostatic drugs may interfere with the bactericidal action of penicillin, it is advisable to avoid giving BIO-MYCIN 200 in conjunction with penicillin.

Adverse Reactions:

Reports of adverse reactions associated with oxytetracycline administration include injection site swelling, restlessness, ataxia, trembling, swelling of eyelids, ears, muzzle, anus and vulva (or scrotum and sheath in males), respiratory abnormalities (labored breathing), frothing at the mouth, collapse and possibly death. Some of these reactions may be attributed either to anaphylaxis (an allergic reaction) or to cardiovascular collapse of unknown cause.

Storage:

Store at controlled room temperature 15°-25°C (59°-77°F). Exposure to colder temperatures may cause cloudiness. Gently warm the product to restore clarity. Use within 12 months of first puncture. Handle aseptically.

Care of Sick Animals:

The use of antibiotics in the management of diseases is based on an accurate diagnosis and an adequate course of treatment. When properly used in the treatment of diseases caused by oxytetracycline susceptible organisms most animals that have been treated with oxytetracycline injection show a noticeable improvement within 24 to 48 hours.

Indications:

BIO-MYCIN 200 is intended for use in the treatment of the following diseases in beef cattle, dairy cattle and swine when due to oxytetracycline-susceptible organisms:

Cattle: In cattle, BIO-MYCIN 200 is indicated in the treatment of pneumonia and shipping fever complex associated with Pasteurella spp. and Haemophilus spp.; infectious bovine keratoconjunctivitis (pinkeye) caused by Moraxella bovis; foot-rot and diphtheria caused by Fusobacterium necrophorum; bacterial enteritis (scours) caused by Escherichia coli; wooden tongue caused by Actinobacillus lignieresii; leptospirosis caused by Leptospira pomona; and wound infections and acute metritis caused by strains of staphylococci and streptococci organisms sensitive to oxytetracycline.

Swine: In swine, BIO-MYCIN 200 is indicated in the treatment of bacterial enteritis (scours, colibacillosis) caused by Escherichia coli; pneumonia caused by Pasteurella multocida; and leptospirosis caused by Leptospira pomona.

In sows, BIO-MYCIN 200 is indicated as an aid in the control of infectious enteritis (baby pig scours, colibacillosis) in suckling pigs caused by Escherichia coli.

Dosage:

Cattle: BIO-MYCIN 200 is to be administered by intramuscular, subcutaneous, or intravenous injection. Intramuscular administration is not recommended according to Beef Quality Assurance Guidelines.

A single dosage of 9 milligrams of BIO-MYCIN 200 per pound of body weight administered intramuscularly or subcutaneously is recommended in the treatment of the following conditions: 1) bacterial pneumonia caused by Pasteurella spp. (shipping fever) in calves and yearlings, where retreatment is impractical due to husbandry conditions, such as cattle on range, or where their repeated restraint is inadvisable; 2) infectious bovine keratoconjunctivitis (pinkeye) caused by Moraxella bovis.

Discontinue treatment at least 28 days prior to slaughter of cattle. Milk taken from animals during treatment and for 96 hours after the last treatment must not be used for food.

BIO-MYCIN 200 can also be administered by intravenous, subcutaneous, or intramuscular injection at a level of 3 to 5 milligrams of oxytetracycline per pound of body weight per day. In the treatment of severe foot-rot and advanced cases of other indicated diseases, a dosage level of 5 milligrams per pound of body weight per day is recommended. Treatment should be continued 24 to 48 hours following remission of disease signs; however, not to exceed a total of four consecutive days. Consult your veterinarian if improvement is not noted within 24 to 48 hours of the beginning of treatment.

Swine: In swine a single dosage of 9 milligrams of BIO-MYCIN 200 per pound of body weight administered intramuscularly is recommended in the treatment of bacterial pneumonia caused by Pasteurella multocida in swine, where retreatment is impractical due to husbandry conditions or where repeated restraint is inadvisable.

Discontinue treatment 28 days prior to slaughter of swine.

BIO-MYCIN 200 can also be administered by intramuscular injection at a level of 3 to 5 milligrams of oxytetracycline per pound of body weight per day.

Treatment should be continued 24 to 48 hours following remission of disease signs; however, not to exceed a total of four consecutive days. Consult your veterinarian if improvement is not noted within 24 to 48 hours of the beginning of treatment.

For sows, administer once intramuscularly 3 milligrams of oxytetracycline per pound of body weight approximately 8 hours before farrowing or immediately after completion of farrowing.

For swine weighing 25 lb of body weight and under, BIO-MYCIN 200 should be administered undiluted for treatment at 9 mg/lb but should be administered diluted for treatment at 3 or 5 mg/lb.

Directions for Use:

BIO-MYCIN 200 is intended for use in the treatment of disease due to oxytetracycline susceptible organisms in beef cattle, dairy cattle and swine. A thoroughly cleaned, sterile needle and syringe should be used for each injection (needles and syringes may be sterilized by boiling in water for 15 minutes). In cold weather, BIO-MYCIN 200 should be warmed to room temperature before administration to animals. Before withdrawing the solution from the bottle, disinfect the rubber cap on the bottle with a suitable disinfectant, such as 70% alcohol. The injection site should be similarly cleaned with the disinfectant. Needles of 16 to 18 gauge and 1 to 1½ inches long are adequate for intramuscular injections. Needles 2 to 3 inches are recommended for intravenous use.

Intramuscular Administration:

Intramuscular injections should be made by directing the needle of suitable gauge and length into the fleshy part of a thick muscle in the neck region; avoid blood vessels and major nerves. Before injecting the solution, pull back gently on the plunger. If blood appears in the syringe, a blood vessel has been entered; withdraw the needle and select a different site. In cattle, intramuscular administration is not recommended according to Beef Quality Assurance Guidelines. No more than 10 mL should be injected intramuscularly at any one site in adult beef cattle and dairy cattle, and not more than 5 mL per site in adult swine; rotate injection sites for each succeeding treatment. The volume administered per injection site should be reduced according to age and body size so that 1 to 2 mL per site is injected in small calves.

Subcutaneous Administration:

Subcutaneous injections in beef cattle and dairy cattle should be made by directing the needle of suitable gauge and length through the loose folds of the neck skin in front of the shoulder. Care should be taken to ensure that the tip of the needle has penetrated the skin but is not lodged in muscle. Before injecting the solution, pull back gently on the plunger. If blood appears in the syringe, a blood vessel has been entered; withdraw the needle and select a different site. The solution should be injected slowly into the area between the skin and muscles.

No more than 10 mL should be injected subcutaneously at any one site in adult beef cattle and dairy cattle; rotate injection sites for each succeeding treatment. The volume administered per injection site should be reduced according to age and body size so that 1 to 2 mL per site is injected in small calves.

Intravenous Administration:

BIO-MYCIN 200 (oxytetracycline injection) may be administered intravenously to beef cattle and dairy cattle. As with all highly concentrated materials, BIO-MYCIN 200 should be administered slowly by the intravenous route.

Preparation of the Animal for Injection:

1. Approximate location of vein. The jugular vein runs in the jugular groove on each side of the neck from the angle of the jaw to just above the brisket and slightly above and to the side of the windpipe. (See Fig. I).
2. Restraint. A stanchion or chute is ideal for restraining the animal. With a halter, rope, or cattle leader (nose tongs), pull the animal’s head around the side of the stanchion, cattle chute, or post in such a manner to form a bow in the neck (See Fig. II), then snub the head securely to prevent movement. By forming the bow in the neck, the outside curvature of the bow tends to expose the jugular vein and make it easily accessible. Caution: Avoid restraining the animal with a tight rope or halter around the throat or upper neck which might impede blood flow. Animals that are down present no problem as far as restraint is concerned.
3. Clip hair in area where injection is to be made (over the vein in the upper third of the neck). Clean and disinfect the skin with alcohol or other suitable antiseptic.

Fig. I
Fig. I

Figure II

Entering the Vein and Making the Injection:

1. Raise the vein. This is accomplished by tying the choke rope tightly around the neck close to the shoulder. The rope should be tied in such a way that it will not come loose and so that it can be untied quickly by pulling the loose end (See Fig. II). In thick-necked animals, a block of wood placed in the jugular groove between the rope and the hide will help considerably in applying the desired pressure at the right point. The vein is a soft flexible tube through which the blood flows back to the heart. Under ordinary conditions, it cannot be seen or felt with the fingers. When the flow of blood is blocked at the base of the neck by the choke rope, the vein becomes enlarged and rigid because of the back pressure. If the choke rope is sufficiently tight, the vein stands out and can be easily seen and felt in thin-necked animals. As a further check in identifying the vein, tap it with the fingers in front of the choke rope. Pulsations that can be seen or felt with the fingers in front of the point being tapped will confirm the fact that the vein is properly distended. It is impossible to put the needle into the vein unless it is distended. Experienced operators are able to raise the vein simply by hand pressure, but the use of a choke rope is more certain.
2. Inserting the needle. This involves three distinct steps. First, insert the needle through the hide. Second, insert the needle into the vein. This may require two or three attempts before the vein is entered. The vein has a tendency to roll away from the point of the needle, especially if the needle is not sharp. The vein can be steadied with the thumb and finger of one hand. With the other hand, the needle point is placed directly over the vein, slanting it so that its direction is along the length of the vein, either toward the head or toward the heart. Properly positioned this way, a quick thrust of the needle will be followed by a spurt of blood through the needle, which indicates that the vein has been entered. Third, once in the vein, the needle should be inserted along the length of the vein all the way to the hub, exercising caution to see that the needle does not penetrate the opposite side of the vein. Continuous steady flow of blood through the needle indicates that the needle is still in the vein. If blood does not flow continuously, the needle is out of the vein (or clogged) and another attempt must be made. If difficulty is encountered, it may be advisable to use the vein on the other side of the neck.
3. While the needle is being placed in proper position in the vein, an assistant should get the medication ready so that the injection can be started without delay after the vein has been entered.
4. Making the injection. With the needle in position as indicated by continuous flow of blood, release the choke rope by a quick pull on the free end. This is essential - the medication cannot flow into the vein while it is blocked. Immediately connect the syringe containing BIO-MYCIN 200 to the needle and slowly depress the plunger. If there is resistance to depression of the plunger, this indicates that the needle has slipped out of the vein (or is clogged) and the procedure will have to be repeated. Watch for any swelling under the skin near the needle, which would indicate that the medication is not going into the vein. Should this occur, it is best to try the vein on the opposite side of the neck.
5. Removing the needle. When injection is complete, remove needle with straight pull. Then apply pressure over area of injection momentarily to control any bleeding through needle puncture, using cotton soaked in alcohol or other suitable antiseptic.

How Supplied:

BIO-MYCIN 200 is available in 100-mL, 250-mL, and 500-mL bottles containing 200 mg oxytetracycline per mL

NDC 0010-4753-01 - 100 mL

NDC 0010-4753-02 - 250 mL

NDC 0010-4753-03 - 500 mL

Not For Human Use.

BIO-MYCIN is a registered trademark of Boehringer Ingelheim Animal Health USA Inc.

© 2023 Boehringer Ingelheim Animal Health USA Inc. All rights reserved

1000004966

3495113-13

Rev. 04/2023

Principal Display Panel – Container Label 500 mL

NDC 0010-4753-03

Bio-Mycin® 200

(oxytetracycline injection)

Antibiotic

Caution: Federal law restricts this drug to use by or on the order of a licensed veterinarian.

Each mL contains 200 mg of oxytetracycline.

For the treatment of disease in beef cattle, dairy cattle and swine.

For animal use only

Net Contents: 500 mL

Approved by FDA under ANADA # 200-008